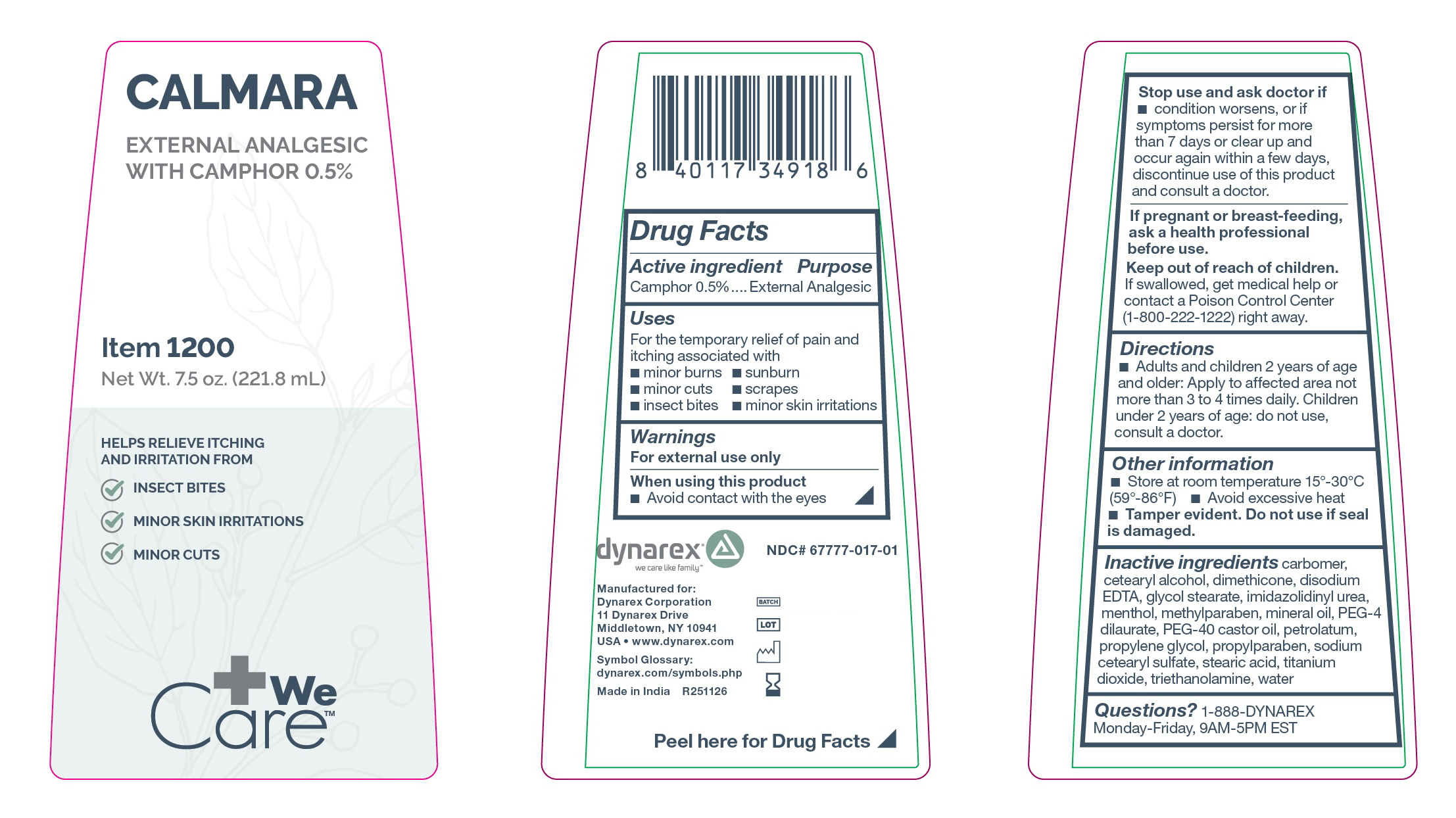 DRUG LABEL: Calmara
NDC: 67777-017 | Form: LOTION
Manufacturer: Dynarex Corporation
Category: otc | Type: HUMAN OTC DRUG LABEL
Date: 20260116

ACTIVE INGREDIENTS: CAMPHOR (NATURAL) 0.5 mg/100 mL
INACTIVE INGREDIENTS: PETROLATUM; MINERAL OIL; PEG-40 CASTOR OIL; PROPYLPARABEN; EDETATE DISODIUM; GLYCOL STEARATE; MENTHOL; WATER; PEG-4 DILAURATE; METHYLPARABEN; PROPYLENE GLYCOL; STEARIC ACID; TRIETHANOLAMINE; IMIDAZOLIDINYL UREA; CARBOMER 940; SODIUM CETEARYL SULFATE; CETEARYL ALCOHOL; DIMETHICONE

1200 Calmara

Active ingredient

Camphor 0.5%

Purpose

External Analgesic

Uses

For temporary relief of pain and itching associated with

• minor burns

• minor cuts

• insect bites

• sunburn

• scrapes

• minor skin irritations

Warnings

For external use only

When using this product

• Avoid contact with the eyes

Stop use and ask a doctor if

• condition worsens, or if symptoms persist for more than 7 days or clear up and occur again within a few days, discontinue use of this product and consult a doctor.

PREGNANCY OR BREAST FEEDING

If pregnant or breast-feeding, ask a health professional before use.

Keep out of reach of children

If swallowed, get medical help or contact a Poison Control Center (1-800-222-1222) right away.

Directions

• Adults and children 2 years of age and older: Apply to affected area not more than 3 to 4 times daily. Children under 2 years of age: do not use, consult a doctor.

Other information

• Store at room temperature 15°-30°C (59°-86°F)

• Avoid excessive heat

• Tamper evident. Do not use if seal is damaged.

Inactive ingredients

carbomer, cetearyl alcohol, dimethicone, disodium EDTA, glycol stearate, imidazolidinyl urea, menthol, methylparaben, mineral oil, PEG-4 dilaurate, PEG-40 castor oil, petrolatum, propylene glycol, propylparaben, sodium cetearyl sulfate, stearic acid, titanium dioxide, triethanolamine, water

Questions?

1-888-DYNAREX Monday-Friday, 9AM-5PM EST